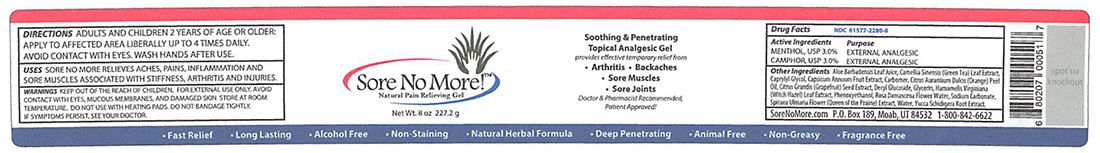 DRUG LABEL: SORE NO MORE
NDC: 61577-2280 | Form: GEL
Manufacturer: SOMBRA COSMETICS INC.
Category: otc | Type: HUMAN OTC DRUG LABEL
Date: 20250529

ACTIVE INGREDIENTS: MENTHOL 0.03 g/1 g; CAMPHOR (SYNTHETIC) 0.03 g/1 g
INACTIVE INGREDIENTS: ALOE VERA LEAF; CAPSICUM; CARBOMER HOMOPOLYMER TYPE C; DECYL GLUCOSIDE; WATER; GRAPEFRUIT SEED OIL; GREEN TEA LEAF; ORANGE PEEL; FILIPENDULA ULMARIA FLOWER; ROSA CENTIFOLIA FLOWER OIL; SODIUM HYDROXYMETHYLGLYCINATE; GLYCERIN; WITCH HAZEL; YUCCA SCHIDIGERA ROOT

SORE NO MORE

Active Ingredients

Menthol USP 3%

Camphor USP 3%

Purpose

PurposeExternal Analgesic

Keep out of reach of children

Uses

Temporarily relieves minor aches, pains, inflammation and sor muscles associated with stiffness, arthritis, and injuries

Warnings

For external use only. Avoid contact with eyes, mucous membranes, damaged skin. Do not use with heating pads, avoid bandaging tightly.

Stop use and ask doctor if: symptoms persist

Directions

adults and children 2 years of age and older: apply to affected area liberally up to 4 times daily. Avoid contact with eyes. Wash hands after use.

Inactive Ingredients

Aloe Barbadensis Leaf Juice, Camellia Sinensis
(Green Tea) Leaf Extract, Caprylyl Glycol, Capsicum Annuum Fruit
Extract, Carbomer, Citrus Aurantium Dulcis (Orange) Peel Oil,
Citrus Grandis (Grapefruit) Seed Extract, Decyl Glucoside, Glycerin,
Hamamelis Virginiana (Witch Hazel) Leaf Extract, Phenoxyethanol,
Purified Water, Rosa Damascena Flower Water, Sodium Carbonate,
Spiraea Ulmaria Flower (Queen of the Prairie) Extract, Yucca
Schidigera Root Extract

Questions or Comments

1-800-842-6622